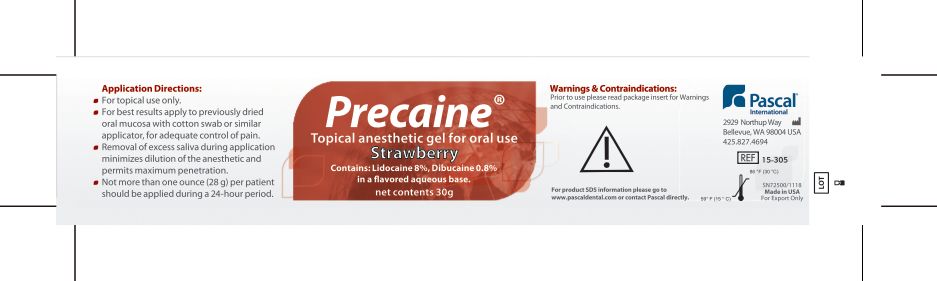 DRUG LABEL: Precaine
NDC: 10866-0062 | Form: GEL
Manufacturer: Pascal Company, Inc.
Category: prescription | Type: HUMAN PRESCRIPTION DRUG LABEL
Date: 20251210

ACTIVE INGREDIENTS: LIDOCAINE 80 mg/1 g; DIBUCAINE 8 mg/1 g

Precaine Anesthetic Gel

DOSAGE FORMS AND STRENGTHS

Contains: Lidocaine 8%, Dibucaine 0.8%

In a flavored aqueous base.

Net Contents 30g

DOSAGE AND ADMINISTRATION

Application Directions:

- For topical use only
- For best results apply to previously dried oral mucosa with cotton swab or similar applicator for adequate control of pain.
- Removal of excess saliva during application minimizes dilution of the anesthetic and permits maximum penetration.
- Not more than one ounce (28g) per patient should be applied during a 24 hour period.

WARNINGS

Recommended dosage should not be exceeded due to possible side effects. Keep out of the reach of children. For professional use only. Do not use in the eyes. Avoid swallowing.

CONTRAINDICATIONS

Precaine is contraindicated in patients with known hypersensitivity to amine or quinoline type anesthetics.

OTHER SAFETY INFORMATION

For product MSDS information please go to www.pascaldental.com or contact Pascal directly.

PACKAGE LABEL

Precaine

Topical Anesthetic Gel for oral use

Strawberry